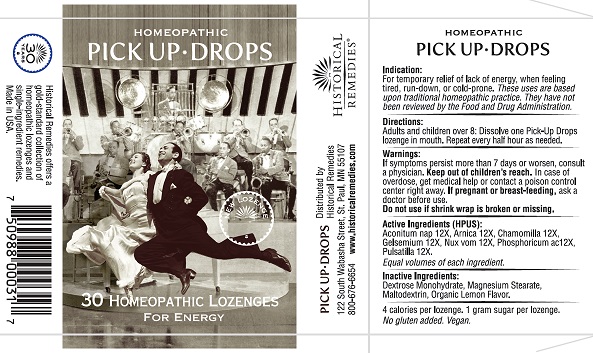 DRUG LABEL: Homeopathic Pick Up Drops
NDC: 57556-007 | Form: LOZENGE
Manufacturer: HISTORICAL REMEDIES LLP.
Category: homeopathic | Type: HUMAN OTC DRUG LABEL
Date: 20251007

ACTIVE INGREDIENTS: PHOSPHORIC ACID 12 [hp_X]/1 1; PULSATILLA VULGARIS WHOLE 12 [hp_X]/1 1; ACONITUM NAPELLUS WHOLE 12 [hp_X]/1 1; STRYCHNOS NUX-VOMICA SEED 12 [hp_X]/1 1; GELSEMIUM SEMPERVIRENS ROOT 12 [hp_X]/1 1; MATRICARIA CHAMOMILLA 12 [hp_X]/1 1; ARNICA MONTANA WHOLE 12 [hp_X]/1 1
INACTIVE INGREDIENTS: DEXTROSE MONOHYDRATE; MAGNESIUM STEARATE; MALTODEXTRIN; LEMON OIL

Homeopathic Pick Up Drops

Indications

For temporary relief of lack of energy, when feeling tired, run-down, or cold-prone. These uses are based upon traditional homeopathic practice. They have not been reviewed by the Food and Drug Administration.

Directions

Adults and children over 8: Dissolve one Pick-Up Drops lozenge in mouth. Repeat every half hour as needed.

Warnings

If symptoms persist more than 7 days or worsen, consult a physician. Keep out of children's reach.In case of overdose, get medical help or contact a poison control center right away. If pregnant or breast-feeding,ask a doctor before use.

Do not use if shrink wrap is broken or missing.

Active ingredients

Aconitum nap 12X, Arnica 12X, Chamomilla 12X, Gelsemium 12X, Nux vom 12X, Phosphoricum ac12X, Pulsatilla 12X.

Inactive ingredients

Dextrose Monohydrate, Magnesium Stearate, Maltodextrin, Organic Vanilla Flavor.

4 calories per lozenge. 1 gram sugar per lozenge.

No gluten added.